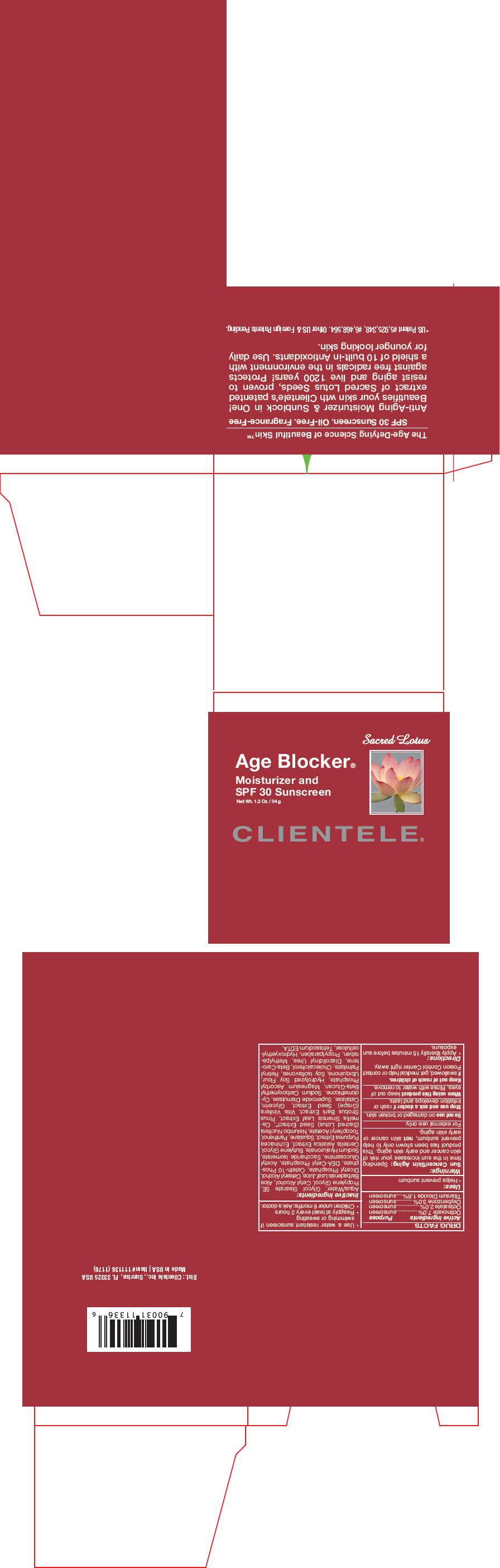 DRUG LABEL: Elastology Age Blocker 
NDC: 64483-030 | Form: CREAM
Manufacturer: Clientele, Inc.
Category: otc | Type: HUMAN OTC DRUG LABEL
Date: 20191209

ACTIVE INGREDIENTS: Octinoxate 7000 mg/1000 g; Octisalate 2000 mg/1000 g; Oxybenzone 3000 mg/1000 g; Titanium Dioxide 1600 mg/1000 g
INACTIVE INGREDIENTS: Water; Glycol Stearate SE; Propylene Glycol; Cetyl Alcohol; Aloe Vera Leaf; Cetostearyl Alcohol; Dihexadecyl Phosphate; Ceteth-10 Phosphate; Diethanolamine Cetyl Phosphate; DISODIUM ACETYL GLUCOSAMINE PHOSPHATE; Saccharide Isomerate; Hyaluronate Sodium; Butylene Glycol; Centella Asiatica; Echinacea Purpurea; Squalane; Panthenol; .Alpha.-Tocopherol Acetate; NELUMBO NUCIFERA SEED; Green Tea Leaf; Pinus Strobus Bark; Vitis Vinifera Seed; Glycerin; CATALASE (BOS TAURUS); Superoxide Dismutase (Saccharomyces Cerevisiae); Cyclomethicone; SODIUM CARBOXYMETHYL .BETA.-GLUCAN (DS 0.65-0.85); Magnesium Ascorbyl Phosphate; SOYBEAN; Ubidecarenone; Soy Isoflavones; Vitamin A Palmitate; Cholecalciferol; Beta Carotene; Methylparaben; Propylparaben; HYDROXYETHYL ETHYLCELLULOSE; Edetate Sodium; Diazolidinyl Urea

Elastology Age Blocker®
Moisturizer & SPF 30 Sunscreen

DRUG FACTS

ACTIVE INGREDIENT

Active Ingredients | Purpose
Octinoxate 7.0% | sunscreen
Octisalate 2.0% | sunscreen
Oxybenzone 3.0% | sunscreen
Titanium Dioxide 1.6% | sunscreen

Uses

- Helps prevent sunburn

Warnings

Sun Cancer/Skin Aging

Spending time in the sun increases your risk of skin cancer and early skin aging. This product has been shown only to help prevent sunburn, not skin cancer or early skin aging.

For external use only.

Do not use on damaged or broken skin.

Stop use and ask a doctor if rash or irritation develops and lasts.

When using this product keep out of eyes. Rinse with water to remove.

Keep out of reach of children.

If swallowed, get medical help or contact Poison Control Center right away.

Directions

- Apply liberally 15 minutes before sun exposure.
- Use a water resistant sunscreen if swimming or sweating
- Reapply at least every 2 hours
- Children under 6 months: Ask a doctor.

Inactive Ingredients

Aqua/Water, Glycol Stearate SE, Propylene Glycol, Cetyl Alcohol, Aloe Barbadensis Leaf Juice, Cetearyl Alcohol, Dicetyl Phosphate, Ceteth-10 Phosphate, DEA-Cetyl Phosphate, Acetyl Glucosamine, Saccharide Isomerate, Sodium Hyaluronate, Butylene Glycol, Centella Asiatica Extract, Echinacea Purpurea Extract, Squalane, Panthenol, Tocopheryl Acetate, Nelumbo Nucifera (Sacred Lotus) Seed Extract*, Camellia Sinensis Leaf Extract, Pinus Strobus Bark Extract, Vitis Vinifera (Grape) Seed Extract, Glycerin, Catalase, Superoxide Dismutase, Cyclomethicone, Sodium Carboxymethyl Beta-Glucan, Magnesium Ascorbyl Phosphate, Hydrolyzed Soy Flour, Ubiquinone, Soy Isoflavones, Retinyl Palmitate, Cholecalciferol, Beta-Carotene, Diazolidinyl Urea, Methylparaben, Propylparaben, Hydroxyethylcellulose, Tetrasodium EDTA.

PRINCIPAL DISPLAY PANEL - 34 g Jar Box

Sacred Lotus

Age Blocker®
Moisturizer and
SPF 30 Sunscreen

Net Wt. 1.2 Oz / 34 g

CLIENTELE®